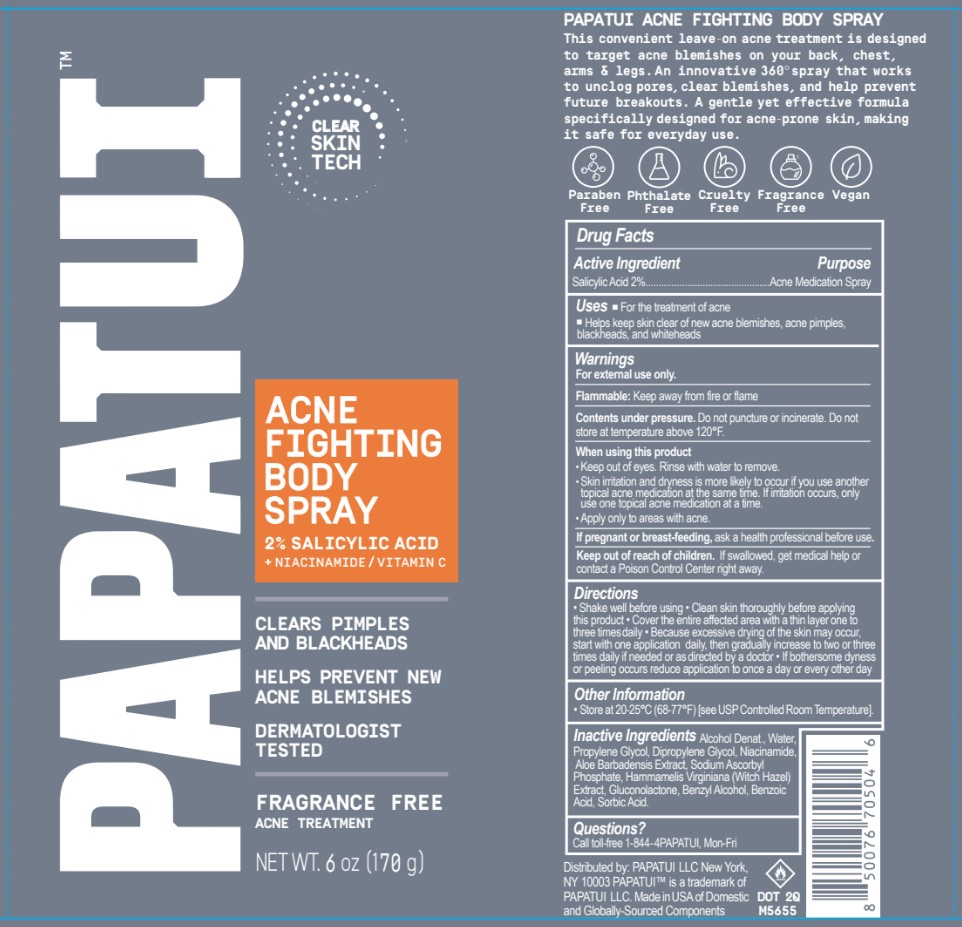 DRUG LABEL: PAPATUI Acne Fighting Body
NDC: 83850-200 | Form: AEROSOL, SPRAY
Manufacturer: PAPATUI, LLC
Category: otc | Type: HUMAN OTC DRUG LABEL
Date: 20250822

ACTIVE INGREDIENTS: SALICYLIC ACID 2 g/100 g
INACTIVE INGREDIENTS: DIPROPYLENE GLYCOL; LEUCONOSTOC/RADISH ROOT FERMENT FILTRATE; ALOE BARBADENSIS LEAF JUICE; BENZYL ALCOHOL; SORBIC ACID; SODIUM ASCORBYL PHOSPHATE; ALCOHOL; WATER; GLUCONOLACTONE; NIACINAMIDE; PROPYLENE GLYCOL; PHENYL FORMATE; GLYCERIN; HAMAMELIS VIRGINIANA (WITCH HAZEL) LEAF WATER

Acne Fighting Body Spray

Drug Facts

Active Ingredient

Active Ingredient | Purpose
Salicylic Acid 2% | Acne Medication Spray

Uses

- For the treatment of acne
- Helps keep skin clear of new acne blemishes, acne pimples, blackheads, and whiteheads

Warnings

For external use only.

Flammable

Flammable: Keep away from fire or flame

Contents under pressure. Do not puncture or incinerate. Do not store at temperature above 120oF.

When using this product

- Keep out of eyes. Rinse with water to remove.
- Skin irritation and dryness is more likely to occur if you use another topical acne medication at the same time. If irritation occurs, only use one topical acne medication at a time.
- Apply only to areas with acne.

PREGNANCY OR BREAST FEEDING

If pregnant or breast-feeding, ask a health professional before use.

Keep out of reach of children. If swallowed, get medical help or contact a Poison Control Center right away.

Directions

- Shake well before using
- Clean skin thoroughly before applying this product
- Cover the entire afflicted area with a thin layer one to three times daily
- Because excessive drying of the skin may occur, start with one application daily, then gradually increase to two or three times daily if needed or as directed by a doctor
- If bothersome dryness or peeling occurs reduce application to once a day or every other day

Other Information

- Store at 20-25oC (68-77oF) [see USP Controlled Room Temperature].

Inactive Ingredients

Alcohol Denat., Water, Propylene Glycol, Dipropylene Glycol, Niacinamide, Aloe Barbadensis Extract, Sodium Ascorbyl Phosphate, Hamamelis Virginiana (Witch Hazel) Extract, Gluconolactone, Benzyl Alcohol, Benzoic Acid, Sorbic Acid.

Questions?

Call toll-free 1-844-4PAPATUI, Mon-Fri

PRINCIPAL DISPLAY PANEL - 170 g Canister

PAPATUI

CLEAR SKIN TECH

ACNE FIGHTING BODY SPRAY

2% SALICYLIC ACID

+ NIACINAMIDE / VITAMIN C

CLEARS PIMPLES

AND BLACKHEADS

HELPS PREVENT NEW

ACNE BLEMISHES

DERMATOLOGIST

TESTED

FRAGRANCE FREE

ACNE TREATMENT

NET WT. 6 oz (170 g)